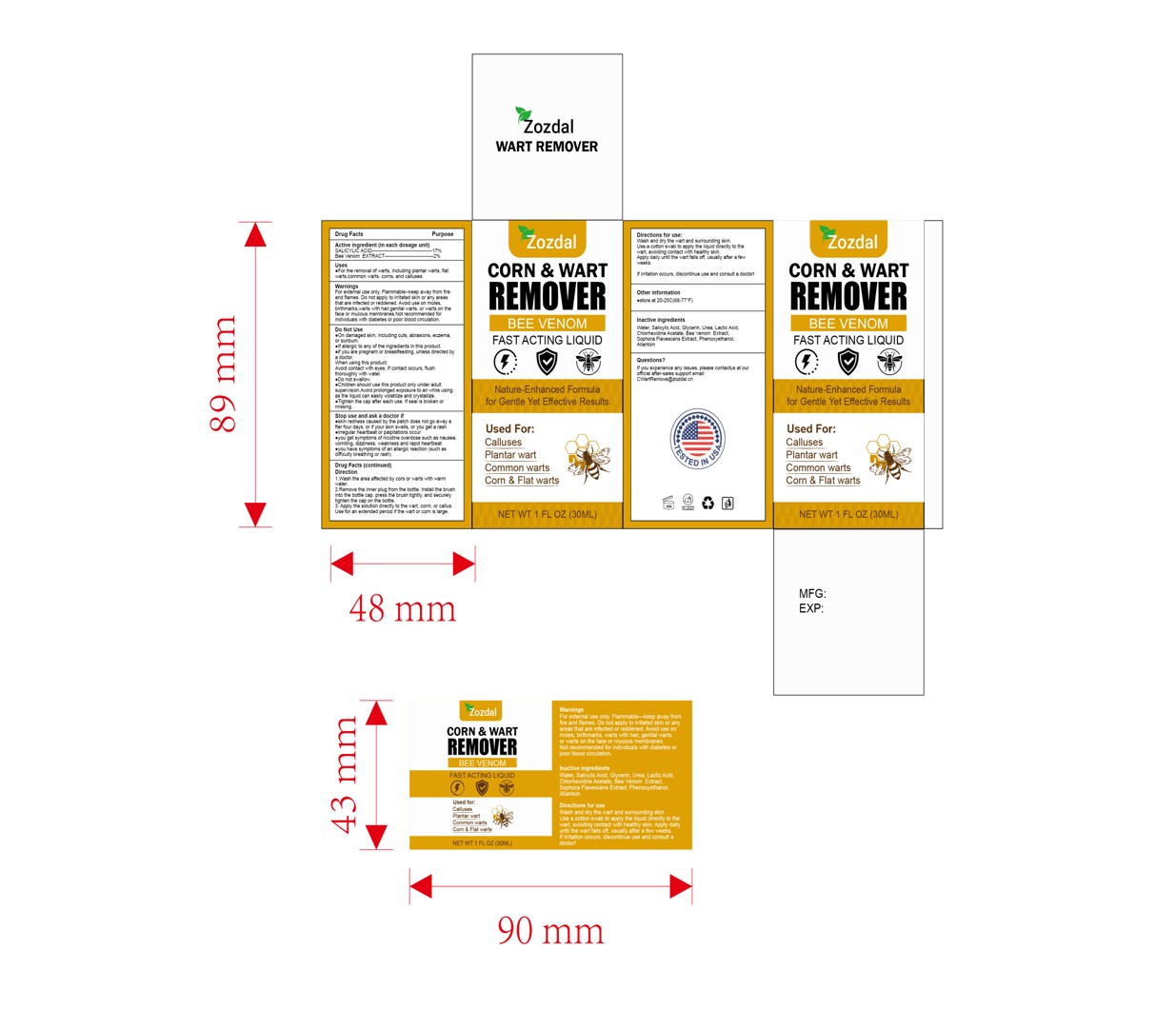 DRUG LABEL: Zozdal Wart Remover
NDC: 84867-018 | Form: LIQUID
Manufacturer: Jiashen International Trade Limited
Category: otc | Type: HUMAN OTC DRUG LABEL
Date: 20250731

ACTIVE INGREDIENTS: SALICYLIC ACID 17 g/100 mL; APIS MELLIFERA VENOM 2 g/100 mL
INACTIVE INGREDIENTS: LACTIC ACID; SOPHORA FLAVESCENS ROOT; CHLORHEXIDINE ACETATE; GLYCERIN; PHENOXYETHANOL; HYDROXYETHYLCELLULOSE; UREA; ALLANTOIN; WATER

ACTIVE INGREDIENT

SALICYLIC ACID 17%
Bee Venom EXTRACT 2%

PURPOSE

wart, corn and callus remover

KEEP OUT OF REACH OF CHILDREN

Please keep the product out of reach of children. lf accidentally ingested, please call the emergency center immediately

WARNINGS

WarningsFor extemal use only, Flammable-keep away from fireand flames.Do not apply to irritated skin or any areasthat are infected or reddened.Avoid usehair.genital warts.,or warts on theface ormucous membranes.Not recommended forindividuals with diabetes or poor blood circulation.

stop use and aska docdor eskthnredhescaused by the patch does not o aay ater lour day,or yourshin snl,or yougeta rasheregular heatbeat or palpaons cuyougetsmiploms of noine overnose such as
nausea.vomiting,dizziness, weakness and rapid heartbeateyou have symptoms of an allergic reaction (such asdificully breathing or rash)

DOSAGE AND ADMINISTRATION

Apply the solution directly to the wart, corm, or callus.Use for an extended period if the wart or corn is large.

INDICATIONS AND USAGE

Direction
Wash he area aeced by ors or watswith wamwaler2.Removethe lmnerplug fiom the boe. hsathebnushino the boe cap.pes he knush ighy, and secureltghen hiecap onhe bole.3.Apythesoluion direclyto
the wart, corm, or callus,Use for an extended period if the wart or corn is large.

INACTIVE INGREDIENT

AQUA
GLYCERIN
LACTIC ACID
UREA
Chlorhexidine Acetate
SOPHORA FLAVESCENS EXTRACT
HYDROXYETHYLCELLULOSE
ALLANTOIN
PHENOXYETHANOL